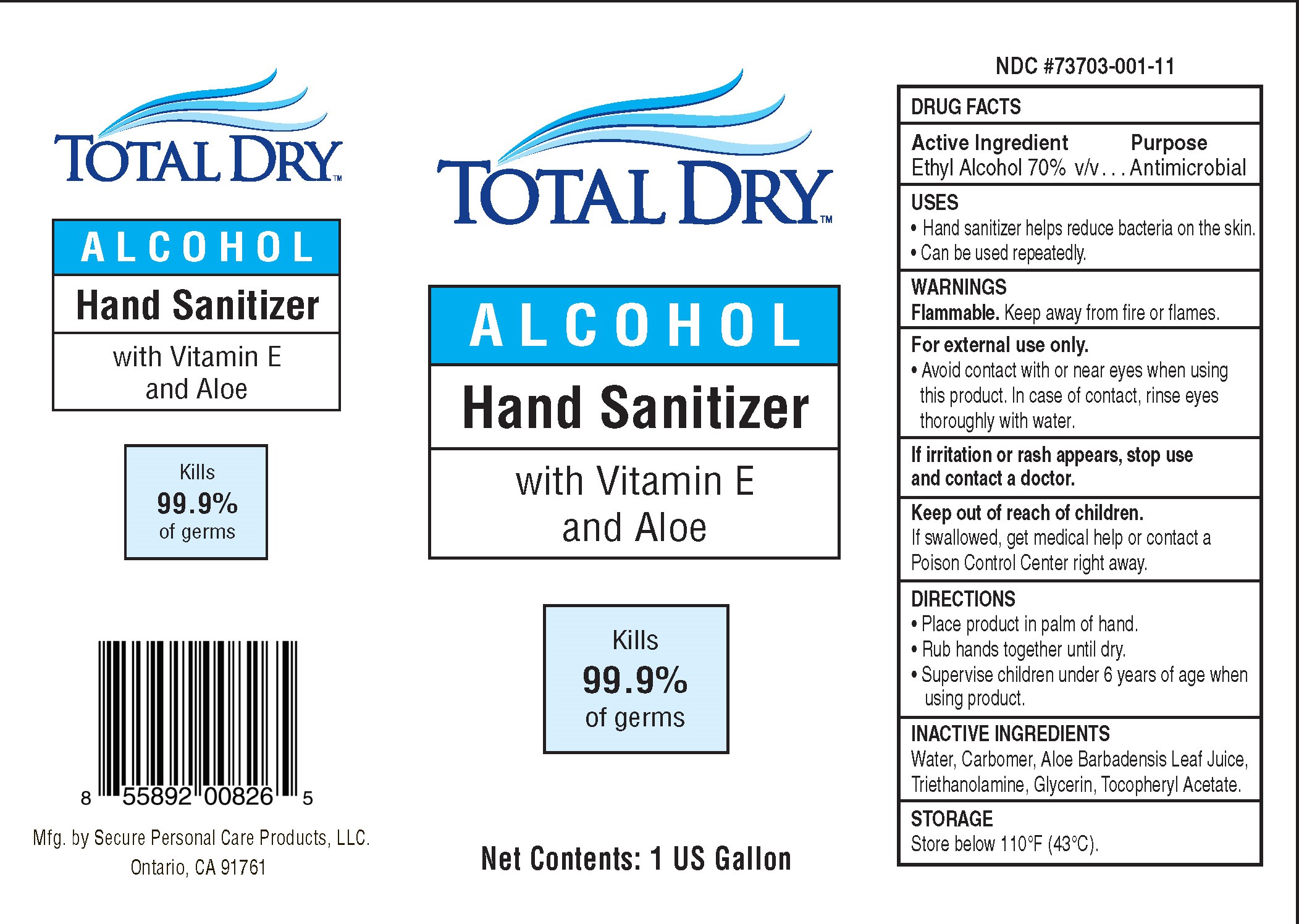 DRUG LABEL: TotalDry Hand Sanitizer
NDC: 73703-001 | Form: SOLUTION
Manufacturer: Secure Personal Care Products LLC
Category: otc | Type: HUMAN OTC DRUG LABEL
Date: 20200503

ACTIVE INGREDIENTS: ALCOHOL .7 mL/1 mL
INACTIVE INGREDIENTS: WATER; CARBOMER HOMOPOLYMER, UNSPECIFIED TYPE; ALOE VERA LEAF; TROLAMINE; GLYCERIN; .ALPHA.-TOCOPHEROL ACETATE

TotalDry™ ALCOHOL Hand Sanitizer

Active Ingredient

Ethyl Alcohol 70% v/v

Purpose

Antimicrobial

USES

- Hand sanitizer helps reduce bacteria on the skin.
- Can be used repeatedly.

WARNINGS

Flammable. Keep away from fire or flames.

For external use only.

- Avoid contact with or near eyes when using this product. In case of contact, rinse eyes thoroughly with water.

STOP USE

If irritation or rash appears, stop use and contact a doctor.

Keep out of reach of children.

If swallowed, get medical help or contact a
Poison Control Center right away.

DIRECTIONS

- Place product in palm of hand.
- Rub hands together until dry.
- Supervise children under 6 years of age when using product.

INACTIVE INGREDIENTS

Water, Carbomer, Aloe Barbadensis Leaf Juice,
Triethanolamine, Glycerin, Tocopheryl Acetate.

STORAGE

Store below 110°F (43°C).